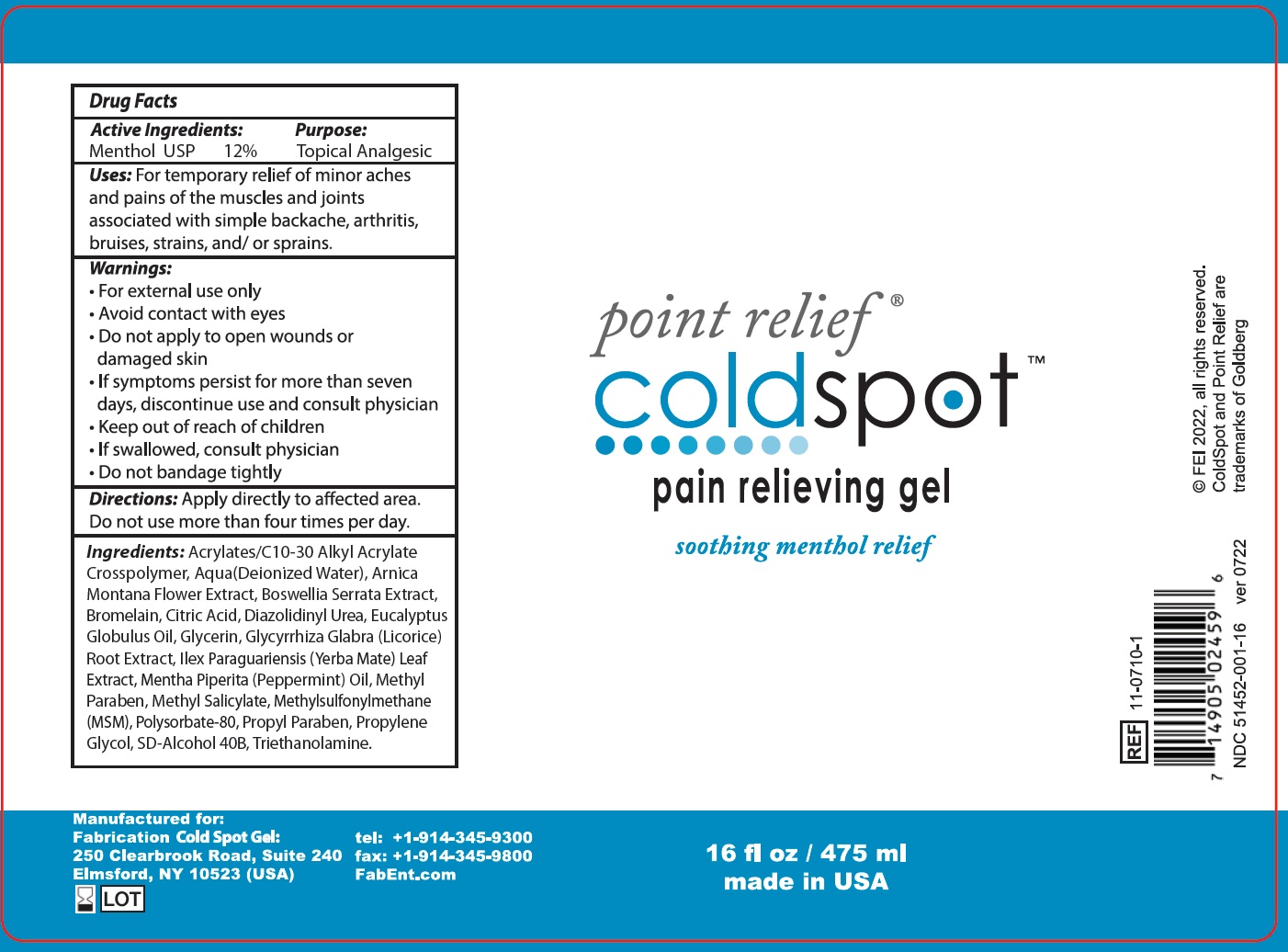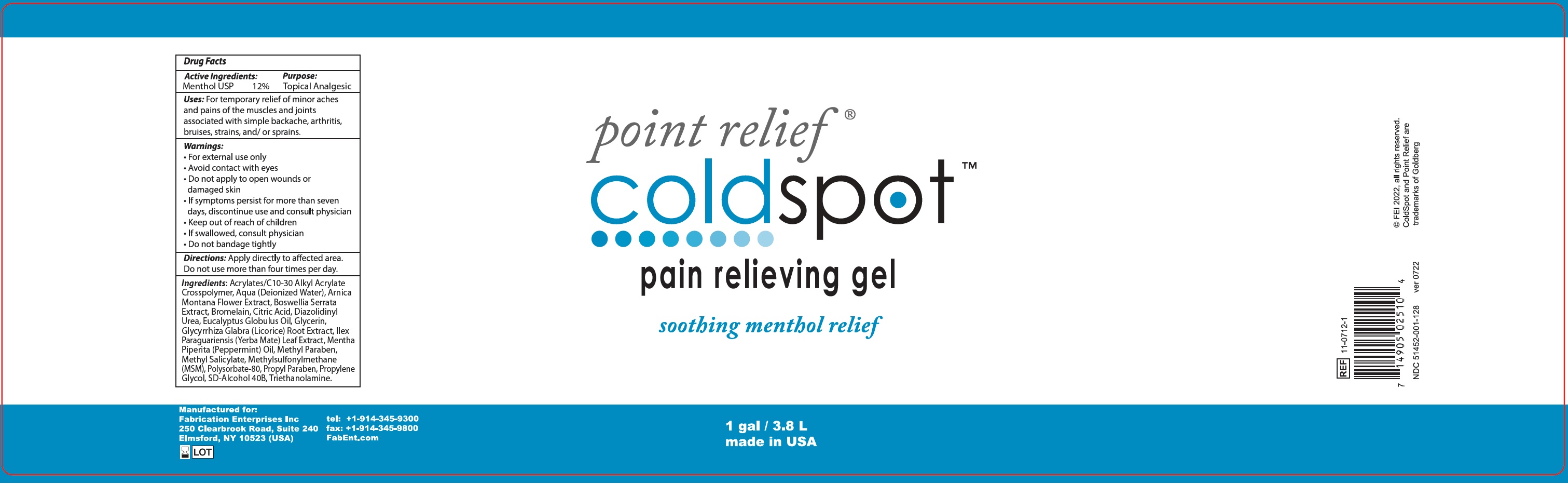 DRUG LABEL: POINT RELIEF COLD SPOT Pain Relieving
NDC: 51452-450 | Form: GEL
Manufacturer: FABRICATION ENTERPRISES
Category: otc | Type: HUMAN OTC DRUG LABEL
Date: 20240207

ACTIVE INGREDIENTS: MENTHOL 120 mg/1 mL
INACTIVE INGREDIENTS: WATER; ARNICA MONTANA FLOWER; INDIAN FRANKINCENSE; BROMELAINS; CITRIC ACID MONOHYDRATE; DIAZOLIDINYL UREA; EUCALYPTUS OIL; GLYCERIN; GLYCYRRHIZA GLABRA; ILEX PARAGUARIENSIS LEAF; PEPPERMINT OIL; METHYLPARABEN; METHYL SALICYLATE; DIMETHYL SULFONE; POLYSORBATE 80; PROPYLPARABEN; PROPYLENE GLYCOL; TROLAMINE

POINT RELIEF COLD SPOT Pain Relieving Gel

Active Ingredients:

Menthol USP 12%

Purpose

Topical Analgesic

Uses:

For temporary relief of minor aches and pains of muscles and joints, associated with simple backache, arthritis, bruises, strains, and/ or sprains.

Warnings:

- For external use only
- Avoid contact with the eyes.
- Do not apply to open wounds or damaged skin
- If symptoms persist for more than seven days, discontinue use and consult physician

Keep out of reach of children.

- If swallowed, consult physician
- Do not bandage tightly.

Directions:

Apply directly to affected area. Do not use more than four times per day.

Ingredients:

Acrylates/C10-30 Alkyl Acrylate Crosspolymer, Aqua(Deionized Water), Arnica Montana Flower Extract, Boswellia Serrata Extract, Bromelain, Citric Acid, Diazolidinyl Urea, Eucalyptus Globulus Oil, Glycerin, Glycyrrhiza Glabra (Licorice) Root Extract, Ilex Paraguariensis (Yerba Mate) Leaf Extract, Mentha Piperita (Peppermint) Oil, Methyl Paraben, Methyl Salicylate, Methylsulfonylmethane (MSM), Polysorbate-80, Propyl Paraben, Propylene Glycol, SD-Alcohol 40B, Triethanolamine.